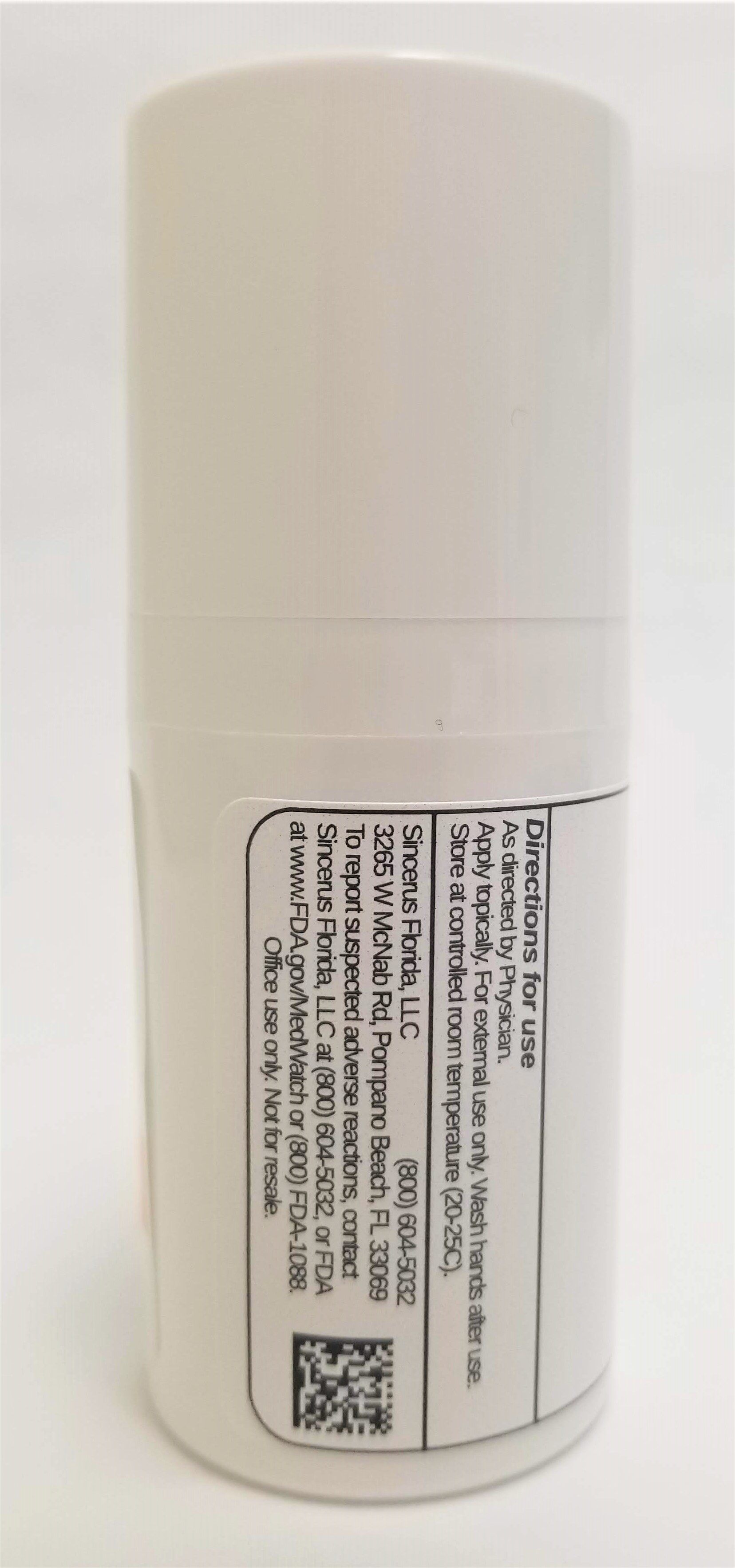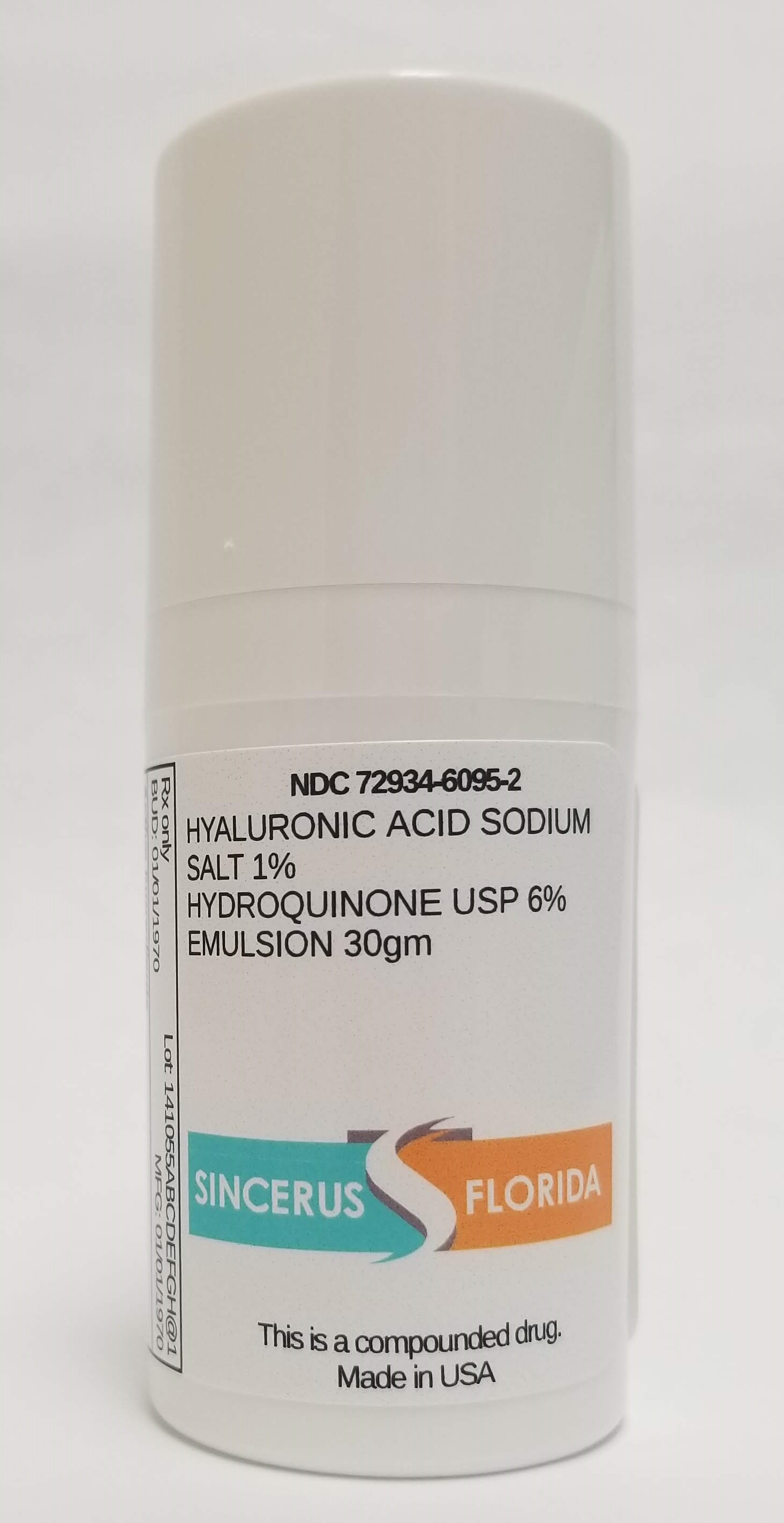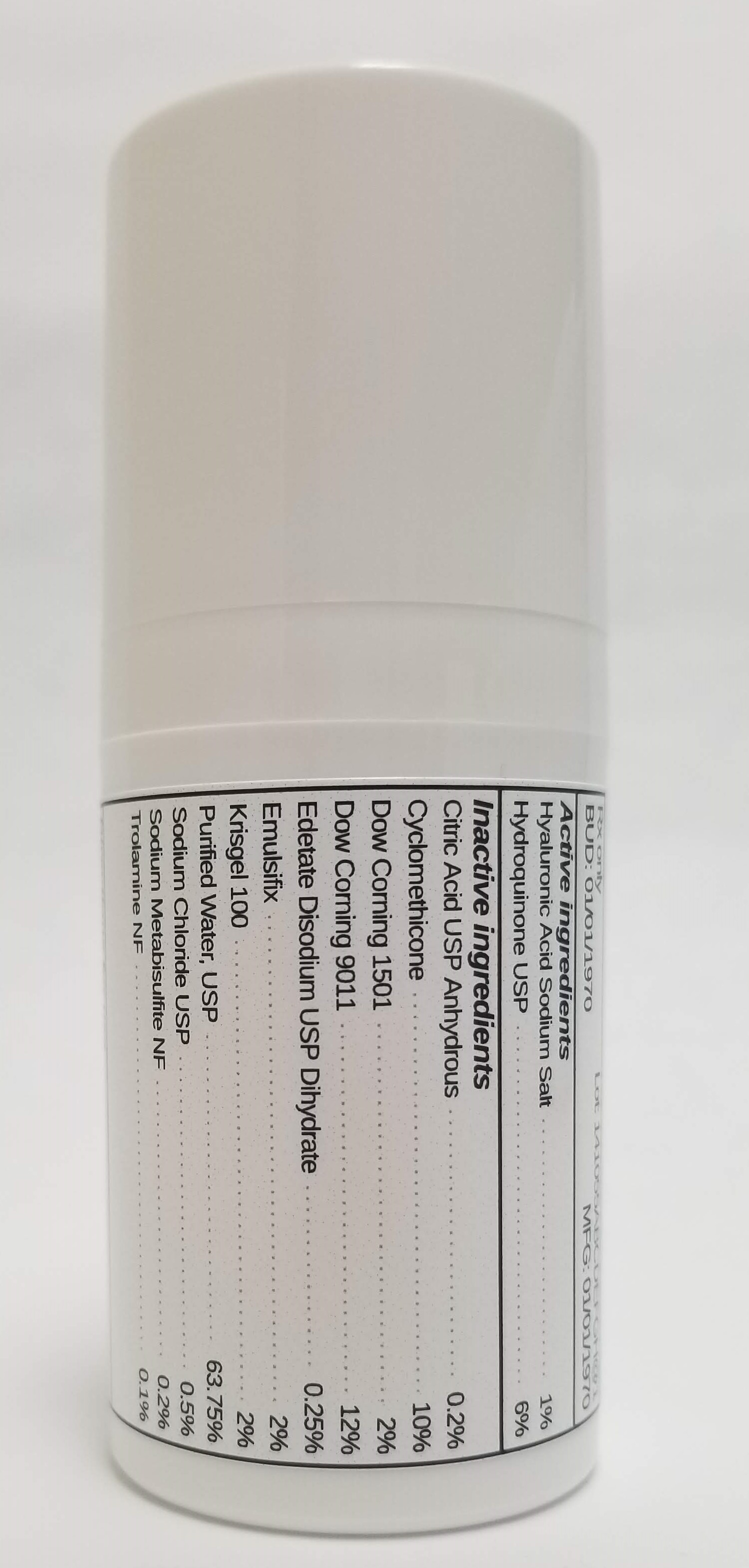 DRUG LABEL: HYALURONIC ACID SODIUM SALT 1% / HYDROQUINONE 6%
NDC: 72934-6095 | Form: EMULSION
Manufacturer: Sincerus Florida, LLC
Category: prescription | Type: HUMAN PRESCRIPTION DRUG LABEL
Date: 20190520

ACTIVE INGREDIENTS: HYDROQUINONE 6 g/100 g; HYALURONATE SODIUM 1 g/100 g

HYALURONIC ACID SODIUM SALT 1% / HYDROQUINONE 6%